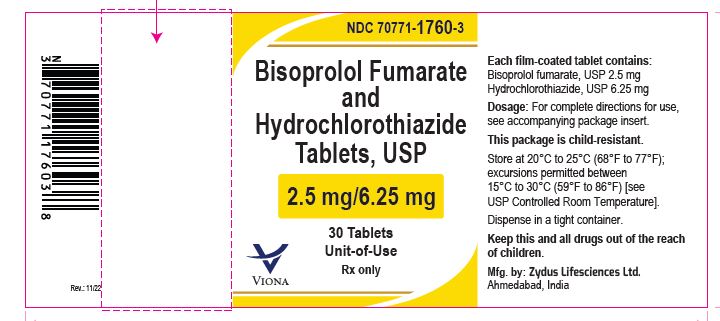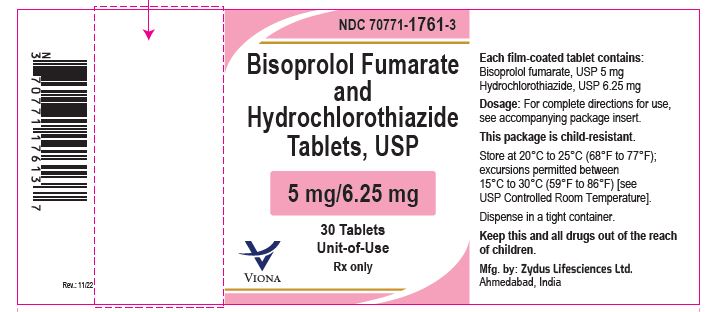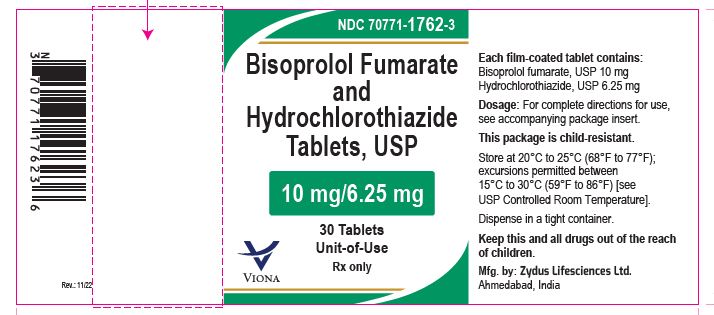 DRUG LABEL: Bisoprolol Fumarate and Hydrochlorothiazide
NDC: 70771-1760 | Form: TABLET, FILM COATED
Manufacturer: Zydus Lifesciences Limited
Category: prescription | Type: HUMAN PRESCRIPTION DRUG LABEL
Date: 20221107

ACTIVE INGREDIENTS: BISOPROLOL FUMARATE 2.5 mg/1 1; HYDROCHLOROTHIAZIDE 6.25 mg/1 1
INACTIVE INGREDIENTS: MICROCRYSTALLINE CELLULOSE 102; BUTYLATED HYDROXYANISOLE; ANHYDROUS DIBASIC CALCIUM PHOSPHATE; MAGNESIUM STEARATE; SILICON DIOXIDE; CROSPOVIDONE (35 .MU.M); HYPROMELLOSE 2910 (6 MPA.S); TITANIUM DIOXIDE; POLYETHYLENE GLYCOL 8000; FERRIC OXIDE YELLOW; FERRIC OXIDE RED

Bisoprolol Fumarate and Hydrochlorothiazide Tablets, USP

PACKAGE LABEL.PRINCIPAL DISPLAY PANEL

NDC 70771-1760-3

Bisoprolol Fumarate and Hydrochlorothiazide Tablets, USP 2.5 mg/6.25 mg

30 Tablets Unit-of-Use

Rx only

NDC 70771-1761-3

Bisoprolol Fumarate and Hydrochlorothiazide Tablets, USP 5 mg/6.25 mg

30 Tablets Unit-of-Use

Rx only

NDC 70771-1762-3

Bisoprolol Fumarate and Hydrochlorothiazide Tablets, USP 10 mg/6.25 mg

30 Tablets Unit-of-Use

Rx only